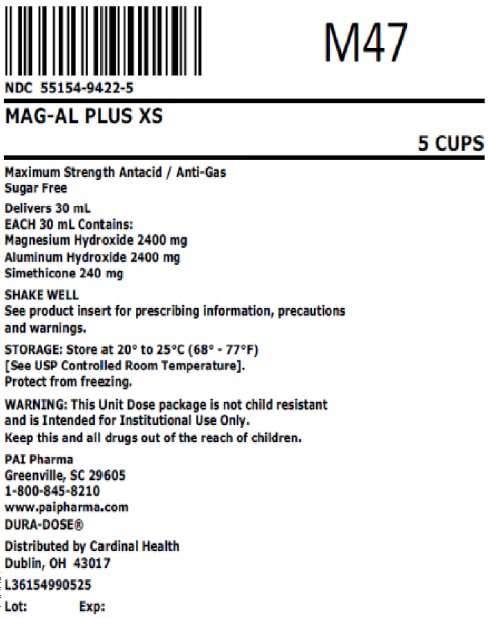 DRUG LABEL: Mag-Al Plus XS
NDC: 55154-9422 | Form: SUSPENSION
Manufacturer: Cardinal Health 107, LLC
Category: otc | Type: HUMAN OTC DRUG LABEL
Date: 20250606

ACTIVE INGREDIENTS: ALUMINUM HYDROXIDE 2400 mg/30 mL; MAGNESIUM HYDROXIDE 2400 mg/30 mL; DIMETHICONE, UNSPECIFIED 240 mg/30 mL
INACTIVE INGREDIENTS: BUTYLPARABEN; HYPROMELLOSE 2910 (4000 MPA.S); PEPPERMINT OIL; CYCLOMETHICONE 4; PROPYLENE GLYCOL; PROPYLPARABEN; WATER; SACCHARIN SODIUM; SORBITOL

Mag-AL Plus XS

Drug Facts

ACTIVE INGREDIENT

PURPOSE

Active ingredients (in each 5 mL = 1 teaspoonful) | Purpose
Aluminum hydroxide (equiv. to dried gel, USP) 400 mg | Antacid
Magnesium hydroxide 400 mg | Antacid
Simethicone 40 mg | Antigas

Uses for the relief of:

- acid indigestion
- heartburn
- sour stomach
- upset stomach due to these symptoms
- pressure and bloating commonly referred to as gas

Warnings

DO NOT USE

Do not take more than 8 teaspoonfuls in a 24-hour period or use the maximum dosage for more than 2 weeks except under the advice and supervision of a physician.

Ask a doctor before use if you have

- kidney disease
- a magnesium-restricted diet

Ask a doctor or pharmacist before use if you are

- presently taking a prescription drug. Antacids may interact with certain prescription drugs.

Stop use and ask a doctor if

- symptoms last more than 2 weeks.

Keep out of reach of children.

Directions

- shake well before using
- do not take more than 8 teaspoonfuls in 24 hours or use the maximum dosage for more than 2 weeks

adults and children 12 years and older | take 2 to 4 teaspoonfuls two times a day or as directed by a physician
children under 12 years | consult a physician

Other information

- each 5 mL contains: magnesium 167 mg, sodium 2.24 mg
- store at controlled room temperature 20° - 25°C (68° - 77°F) [see USP Controlled Room Temperature].
- protect from freezing
- White colored, cherry flavored liquid supplied in the following oral dosage form:

Overbagged with 5 x 30 mL unit dose cups in each bag, NDC 55154-9422-5

WARNING: This Unit Dose package is not child resistant and is Intended for Institutional Use Only. Keep this and all drugs out of the reach of children.

*Maalox is a registered trademark of Novartis Consumer Health, Inc.

Inactive ingredients

Butylparaben, hydroxypropyl methylcellulose, flavoring, propylene glycol, propylparaben, purified water, sodium saccharin, and sorbitol solution.

MANUFACTURED BY

Pharmaceutical
Associates, Inc.
Greenville, SC 29605
www.paipharma.com

Distributed By:

Cardinal Health

Dublin, OH 43017

L36154990525

Principal Display Panel

NDC 55154-9422-5

MAG-AL PLUS XS

5 CUPS